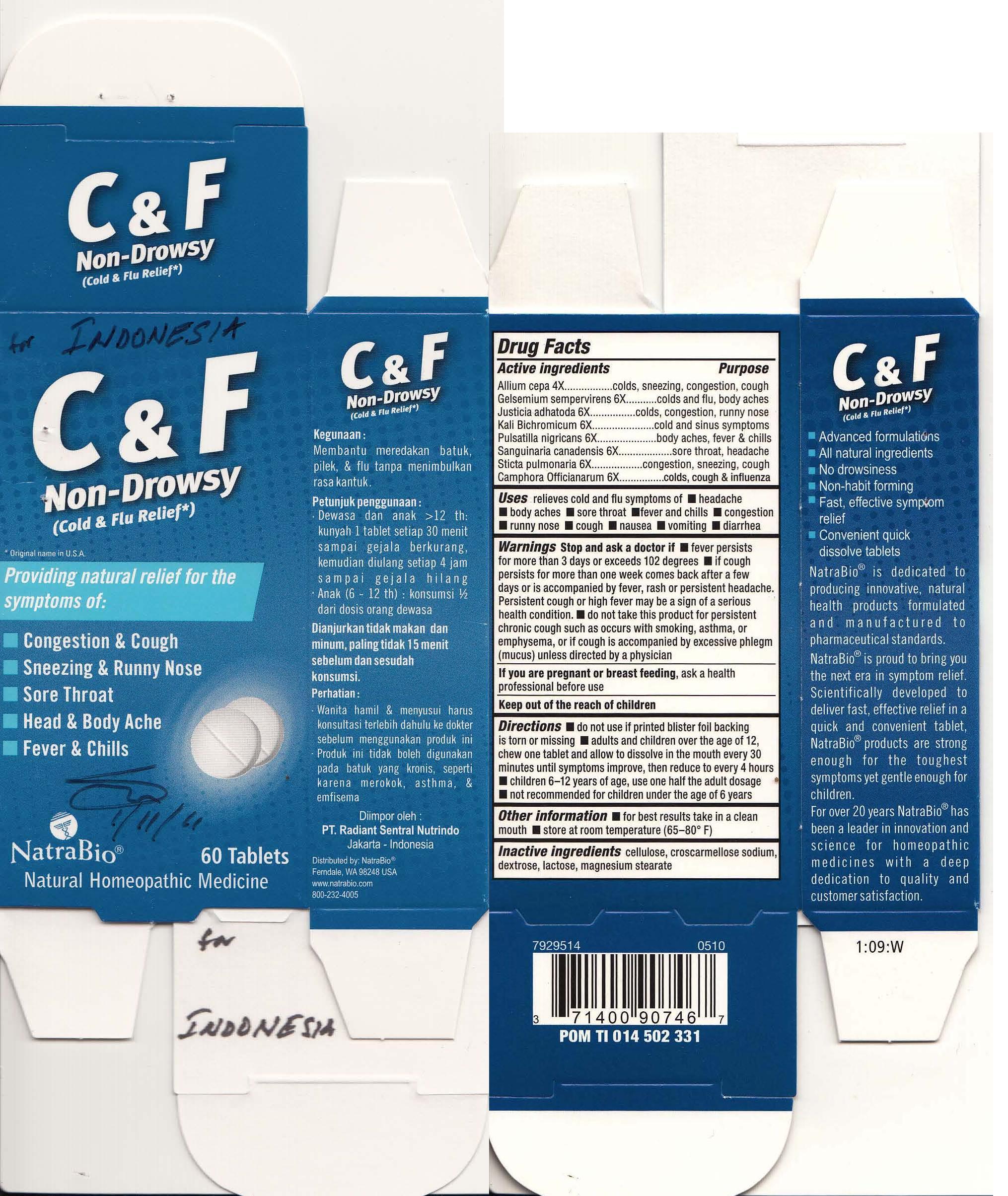 DRUG LABEL: Cold and Flu Relief
NDC: 65808-024 | Form: TABLET
Manufacturer: GMP Laboratories of America, Inc
Category: homeopathic | Type: HUMAN OTC DRUG LABEL
Date: 20150626

ACTIVE INGREDIENTS: ACONITUM NAPELLUS 4 [hp_X]/1 1; ONION 4 [hp_X]/1 1; GELSEMIUM SEMPERVIRENS ROOT 4 [hp_X]/1 1; JUSTICIA ADHATODA LEAF 6 [hp_X]/1 1; POTASSIUM CHROMATE 6 [hp_X]/1 1; PULSATILLA VULGARIS 6 [hp_X]/1 1; SANGUINARIA CANADENSIS ROOT 6 [hp_X]/1 1; LOBARIA PULMONARIA 6 [hp_X]/1 1; CAMPHOR (NATURAL) 6 [hp_X]/1 1
INACTIVE INGREDIENTS: POWDERED CELLULOSE; CROSCARMELLOSE SODIUM; DEXTROSE; LACTOSE; MAGNESIUM STEARATE

Cold and Flu Relief Indonesia

Drug Facts

Active ingredient | Purpose
Aconitum napellus | influenza, colds, fever, congestion
Allium cepa | colds, sneezing, congestion, cough
Gelsemium sempervirens | colds and flu, body aches
Justicia adhatoda | colds, congestion, runny nose
Kali Bichromicum | cold and sinus symptoms
Pulsatilla nigricans | body aches, fever & chills
Sanguinaria canadensis | sore throat, headache
Sticta pulmonaria | congestions, sneezing, cough
Camphora Offcianarum | colds, cough & influenza

Uses

Relieves cold and flu symptoms of

- headache
- body aches
- sore throat
- fever and chills
- congestion
- runny nose
- cough
- nausea
- vomiting
- diarrhea

Warnings

Stop and ask a doctor if

- fever persists for more than 3 days or exceeds 102 degrees
- if cough persists for more than one week, comes back after a few days, or is accompanied by fever, rash or persistent headache. Persistent cough or high fever may be a sign of a serious health condition.
- do not take this product for persistent chronic cough such as occurs with smoking, asthma, or emphysema, or if cough is accompanied by excessive phlegm (mucus) unless directed by a physician

PREGNANCY OR BREAST FEEDING

If pregnant or breast-feeding, ask a health professional before use

Keep out of reach of children. In case of overdose, get medical help or contact a Poison Control Center right away.

Directions

- do not use if printed blister foil backing is torn or missing
- adults and children over the age of 12, chew one tablet and allow to dissolve in the mouth every 30 minutes until symptoms inprove, then reduce to every 4 hours
- children 6-12 use one half the adult dosage
- not recommended for children under the age of 6

Other information

- for best results, take in a clean mouth
- store at room temperature (65-80°F)

Inactive ingredients

cellulose, croscarmellose sodium, dextrose, lactose, mangnesium stearate